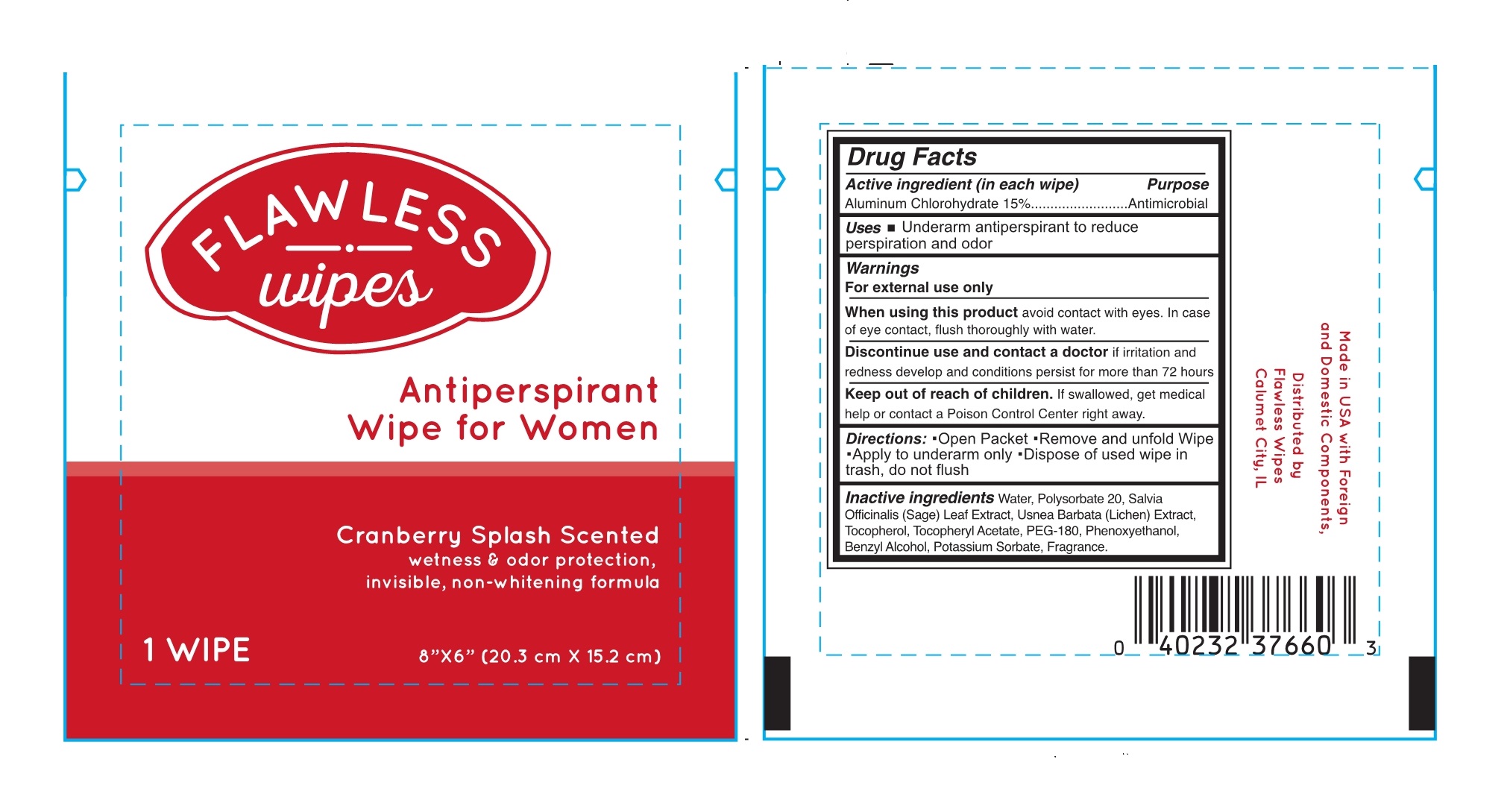 DRUG LABEL: Antiperspirant Wipe for Women
NDC: 71592-001 | Form: SWAB
Manufacturer: FlawlessWipes, LLC
Category: otc | Type: HUMAN OTC DRUG LABEL
Date: 20170717

ACTIVE INGREDIENTS: ALUMINUM CHLOROHYDRATE 15 g/100 g
INACTIVE INGREDIENTS: Water; USNEA BARBATA; TOCOPHEROL; .ALPHA.-TOCOPHEROL ACETATE, DL-; SAGE; POTASSIUM SORBATE; POLYSORBATE 20; PHENOXYETHANOL; BENZYL ALCOHOL; POLYETHYLENE GLYCOL 8000

ACTIVE INGREDIENT

Aluminum Chlorohydrate 15%

Purpose

Antiperspirant

USES

Underarm antiperspirant to reduce perspiration and odor

WARNINGS

- For external use only
- When using this product avoid contact with eyes. in case of eye contact, flush thoroughly with water.
- Discontinue use and contact a doctor if irritation and redness develop and conditions persist for more than 72 hours

KEEP OUT OF REACH OF CHILDREN

If swallowed, get medical help or contact a poison control center right away

DIRECTIONS

Open packet, remove and unfold wipe, apply to underarm only, dispose of used wipe in the trash, do not flush.

Inactive ingredients

Water, polysorbate 20, Salvia Officinalis (Sage) Leaf Extract, Usnea Barbata (Lichen) extract, Tocopherol, Tocopheryl Acetate, PEG-180, Phenoxyethanol, Benzyl Alcohol, Potassium Sorbate, Fragrance